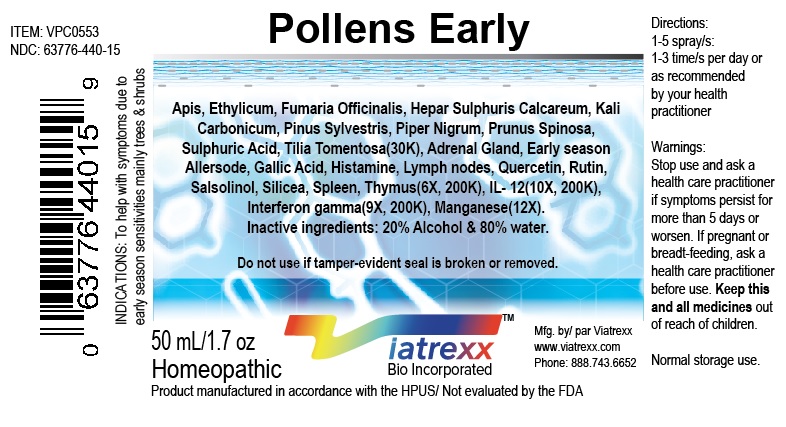 DRUG LABEL: Pollens Early
NDC: 63776-440 | Form: SPRAY
Manufacturer: VIATREXX BIO INCORPORATED
Category: homeopathic | Type: HUMAN OTC DRUG LABEL
Date: 20180111

ACTIVE INGREDIENTS: Interleukin-12 Human 200 [kp_C]/1 mL; Interferon Gamma-1a 200 [kp_C]/1 mL; Sus Scrofa Adrenal Gland 200 [kp_C]/1 mL; Bos Taurus Adrenal Gland 200 [kp_C]/1 mL; Apis Mellifera 30 [kp_C]/1 mL; Fumaria Officinalis Flowering Top 30 [kp_C]/1 mL; Gallic Acid 200 [kp_C]/1 mL; Calcium Sulfide 30 [kp_C]/1 mL; Histamine 200 [kp_C]/1 mL; Potassium Carbonate 30 [kp_C]/1 mL; Bos Taurus Lymph Vessel 200 [kp_C]/1 mL; Sus Scrofa Lymph Vessel 200 [kp_C]/1 mL; Manganese 12 [hp_X]/1 mL; Pinus Sylvestris Sprout 30 [kp_C]/1 mL; Black Pepper 30 [kp_C]/1 mL; Prunus Spinosa Flower Bud 30 [kp_C]/1 mL; Quercetin 200 [kp_C]/1 mL; Rutin 200 [kp_C]/1 mL; Salsolinol 200 [kp_C]/1 mL; Silicon Dioxide 200 [kp_C]/1 mL; Sus Scrofa Spleen 200 [kp_C]/1 mL; Sulfuric Acid 30 [kp_C]/1 mL; Sus Scrofa Thymus 200 [kp_C]/1 mL; Bos Taurus Thymus 200 [kp_C]/1 mL; Bos Taurus Spleen 200 [kp_C]/1 mL; Tilia Tomentosa Bud 30 [kp_C]/1 mL; Fraxinus Americana Pollen 200 [kp_C]/1 mL; Betula Nigra Pollen 200 [kp_C]/1 mL; Juglans Nigra Pollen 200 [kp_C]/1 mL; Ulmus Americana Pollen 200 [kp_C]/1 mL; Quercus Rubra Pollen 200 [kp_C]/1 mL; Fagus Grandifolia Pollen 200 [kp_C]/1 mL; Populus Deltoides Subsp. Deltoides Pollen 200 [kp_C]/1 mL; Carya Alba Pollen 200 [kp_C]/1 mL; Platanus Racemosa Pollen 200 [kp_C]/1 mL; Salix Repens Pollen 200 [kp_C]/1 mL; Acer Saccharum Pollen 200 [kp_C]/1 mL
INACTIVE INGREDIENTS: Alcohol; Water

Pollens Early

Active Ingredients

interleukin-12 human , interferon gamma-1a , sus scrofa adrenal gland , bos taurus adrenal gland , apis mellifera , fumaria officinalis flowering top , gallic acid , calcium sulfide , histamine , potassium carbonate , bos taurus lymph vessel , sus scrofa lymph vessel , manganese , pinus sylvestris sprout , black pepper , prunus spinosa flower bud , quercetin , rutin , salsolinol , silicon dioxide , sus scrofa spleen , sulfuric acid , sus scrofa thymus , bos taurus thymus , bos taurus spleen , tilia tomentosa bud , fraxinus americana pollen , betula nigra pollen , juglans nigra pollen , ulmus americana pollen , quercus rubra pollen , fagus grandifolia pollen , populus deltoides subsp. deltoides pollen , carya alba pollen , platanus racemosa pollen , salix repens pollen and acer saccharum pollen

Purpose:

Adrenal Gland 6X, 200K Adrenal support
Apis 30K Anti-inflammation
Early season Allersode 6X, 200K Immune support
Ethylicum 30K Drainage
Fumaria Officinalis 30K Drainage
Gallic Acid 6X, 200K Immune support
Hepar Sulphuris Calcareum 30K Drainage
Histamine 6X, 200K Ig support
IL- 12 10X, 200K Immune support
Interferon gamma 9X, 200K Immune support
Kali Carbonicum 30K Drainage
Lymph nodes 6X, 200K Immune support
Manganese 12X Regeneration
Pinus Sylvestris 30K Regeneration
Piper Nigrum 30K Drainage
Prunus Spinosa 30K Drainage
Quercetin 6X, 200K Drainage
Rutin 6X, 200K Drainage
Salsolinol 6X, 200K Drainage
Silicea 6X, 200K Drainage
Spleen 6X, 200K Regeneration
Sulphuricum Acidum 30K Drainage
Thymus 6X, 200K Immune support
Tilia Tomentosa 30K Neurological support

Uses

For the temporary support of symptoms related to seasonal spring sensitivities

Warnings

Stop use and ask a health care practitioner if symptoms persist for more than five days or worsen. If pregnant or breastfeeding, ask a health care practitioner before use.

Dosage

1-5 spray(s); 1-3 time(s) per day or as recommended by your health care practitioner.

KEEP OUT OF REACH OF CHILDREN

Keep this and all medicines out of reach of children.

Other Ingredients

20% Alcohol and 80% Water

Other Information

Normal storage use.
Do not use if tamper-evident seal is broken or removed.

Questions

info@viatrexx.com

Principal Display Panel

ITEM: VPC0553
NDC 63776-440-15
Homeopathic remedy
Pollens Early
For the temporary support of symptoms related to seasonal spring sensitivities
Oral spray
50ml 1.7 oz
Viatrexx™ Bio Incorporated
Manufactured by Viatrexx
www.viatrexx.com
Newark, DE 19713

Pollens Early
50 ml
1.7 oz
Viatrexx™ Bio Incorporated
ITEM: VPC0553
NDC: 63776-440-15
INDICATIONS:
For the temporary support of symptoms related to seasonal spring sensitivities
DIRECTIONS:
1-5 spray(s); 1-3 time(s) per day or as recommended by your health care practitioner.
Mfg. for
Viatrexx Bio Incorporated.
www.viatrexx.com
Newark, DE 19713